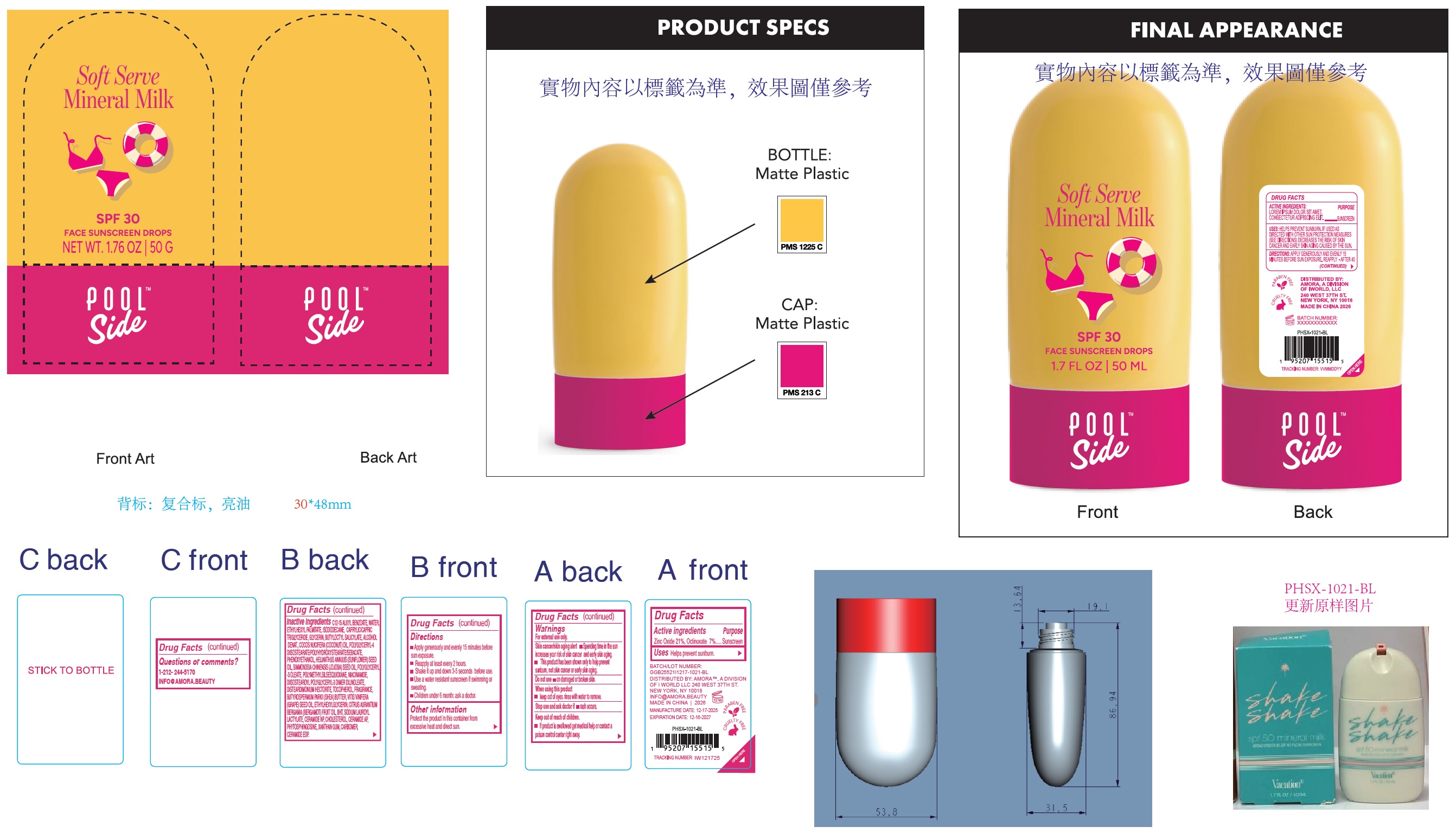 DRUG LABEL: Poolside Soft Serve Mineral Milk SPF 30 Face Sunscreen Drops
NDC: 85179-041 | Form: CREAM
Manufacturer: I World LLC
Category: otc | Type: HUMAN OTC DRUG LABEL
Date: 20260127

ACTIVE INGREDIENTS: ZINC OXIDE 210 mg/1 g; OCTINOXATE 70 mg/1 g
INACTIVE INGREDIENTS: C12-15 ALKYL BENZOATE; WATER; ETHYLHEXYL PALMITATE; ISODODECANE; CAPRYLIC/CAPRIC TRIGLYCERIDE; GLYCERIN; BUTYLOCTYL SALICYLATE; ALCOHOL; COCONUT OIL; POLYGLYCERYL-4 DIISOSTEARATE/POLYHYDROXYSTEARATE/SEBACATE; PHENOXYETHANOL; HELIANTHUS ANNUUS (SUNFLOWER) SEED OIL; JOJOBA OIL; POLYGLYCERYL-3 OLEATE; NIACINAMIDE; DIISOSTEAROYL POLYGLYCERYL-3 DIMER DILINOLEATE; DISTEARDIMONIUM HECTORITE; TOCOPHEROL; SHEA BUTTER; GRAPE SEED OIL; ETHYLHEXYLGLYCERIN; BERGAMOT OIL; BUTYLATED HYDROXYTOLUENE; SODIUM LAUROYL LACTYLATE; CERAMIDE NP; CHOLESTEROL; CERAMIDE AP; PHYTOSPHINGOSINE; XANTHAN GUM; CARBOMER HOMOPOLYMER, UNSPECIFIED TYPE

Poolside Soft Serve Mineral Milk SPF 30 Face Sunscreen Drops

Active ingredient

Zinc Oxide 21%, Octinoxate 7%

Purpose

Sunscreen

Uses

- Helps prevent sunburn.

Warnings

For external use only.
Skin cancer/skin aging alert

- Spending time in the sun increases your risk of skin cancer and early skin aging.
- This product has been shown only to help prevent sunburn, not skin cancer or early skin aging.

Do not use

- on damaged or broken skin.

when using this product

- keep out of eyes. rinse with water to remove.

Stop use and ask a doctor if

- rash occurs.

Keep out of reach of children.

- If product is swallowed get medical help or contact a poison control centre right away.

Directions

- Apply generously and evenly 15 minutes before sun exposure.
- Reapply at least every 2 hours.
- Shake it up and down 3-5 seconds before use.
- Use a water resistant sunscreen if swimming or sweating.
- Children under 6 month: ask a doctor.

Other information

Protect the product in this container from excessive heat and direct sun.

Inactive ingredients

C12-15 ALKYL BENZOATE, WATER, ETHYLHEXYL PALMITATE, ISODODECANE, CAPRYLIC/CAPRIC TRIGLYCERIDE, GLYCERIN, BUTYLOCTYL SALICYLATE, ALCOHOL DENAT., COCOS NUCIFERA (COCONUT) OIL, POLYGLYCERYL-4 DIISOSTEARATE/POLYHYDROXYSTEARATE/SEBACATE, PHENOXYETHANOL, HELIANTHUS ANNUUS (SUNFLOWER) SEED OIL, SIMMONDSIA CHINENSIS (JOJOBA) SEED OIL, POLYGLYCERYL -3 OLEATE, POLYMETHYLSILSESQUIOXANE, NIACINAMIDE, DIISOSTEAROYL POLYGLYCERYL-3 DIMER DILINOLEATE, DISTEARDIMONIUM HECTORITE, TOCOPHEROL, FRAGRANCE, BUTYROSPERMUM PARKII (SHEA) BUTTER, VITIS VINIFERA (GRAPE) SEED OIL, ETHYLHEXYLGLYCERIN, CITRUS AURANTIUM BERGAMIA (BERGAMOT) FRUIT OIL, BHT, SODIUM LAUROYL LACTYLATE, CERAMIDE NP, CHOLESTEROL, CERAMIDE AP, PHYTOSPHINGOSINE, XANTHAN GUM, CARBOMER, CERAMIDE EOP.

Questions or comments?

1-212-244-5170 INFO@AMORA.BEAUTY